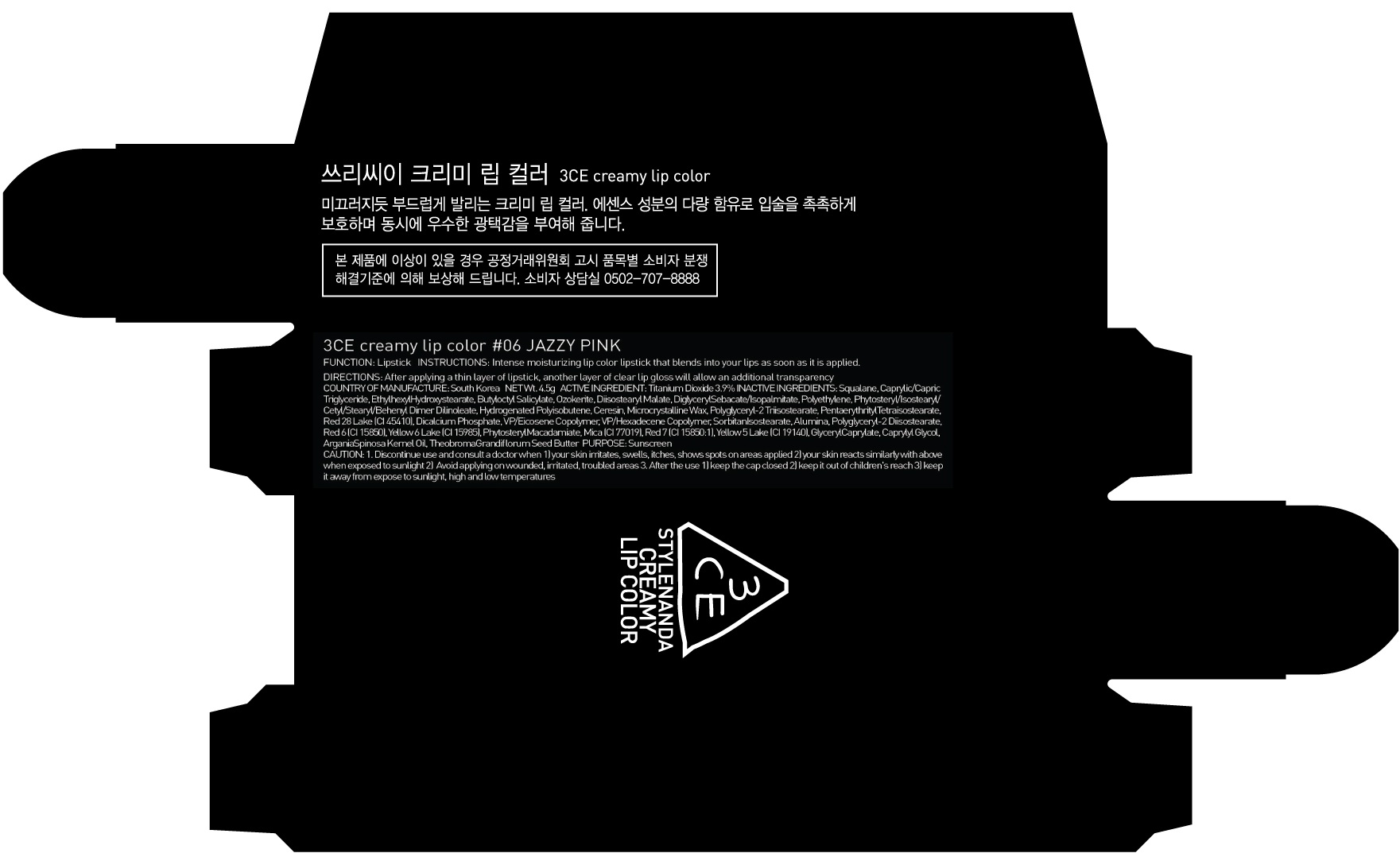 DRUG LABEL: 3CE CRE AMY LIP COLOR 06 JAZZY PINK
NDC: 60764-116 | Form: LIPSTICK
Manufacturer: Nanda Co., Ltd
Category: otc | Type: HUMAN OTC DRUG LABEL
Date: 20161014

ACTIVE INGREDIENTS: Titanium Dioxide 0.17 g/4.5 g
INACTIVE INGREDIENTS: Squalane; Ethylhexyl Hydroxystearate

ACTIVE INGREDIENT

Active Ingredient: Titanium Dioxide 3.9%

INACTIVE INGREDIENT

Inactive Ingredients: Squalane, Caprylic/Capric Triglyceride, Ethylhexyl Hydroxystearate, Butyloctyl Salicylate, Ozokerite, Diisostearyl Malate, DiglycerylSebacate/Isopalmitate, Polyethylene, Phytosteryl/Isostearyl/Cetyl/Stearyl/Behenyl Dimer Dilinoleate, Hydrogenated Polyisobutene, Ceresin, Microcrystalline Wax, Polyglyceryl-2 Triisostearate, PentaerythritylTetraisostearate, Red 28 Lake (CI 45410), Dicalcium Phosphate, VP/Eicosene Copolymer, VP/Hexadecene Copolymer, SorbitanIsostearate, Alumina, Polyglyceryl-2 Diisostearate, Red 6 (CI 15850), Yellow 6 Lake (CI 15985), PhytosterylMacadamiate, Mica (CI 77019), Red 7 (CI 15850:1), Yellow 5 Lake (CI 19140), GlycerylCaprylate, Caprylyl Glycol, ArganiaSpinosa Kernel Oil, Theobroma Grandiflorum Seed Butter

PURPOSE

Purpose: Sunscreen

CAUTION

CAUTION: 1. Discontinue use and consult a doctor when - your skin irritates, swells, itches, shows spots on areas applied - your skin reacts similarly with above when exposed to sunlight 2. Avoid applying on wounded, irritated, troubled areas 3. After the use - keep the cap closed - keep it out of children's reach - keep it away from expose to sunlight, high and low temperatures

DESCRIPTION

INSTRUCTIONS: Intense moisturizing lip color lipstick that blends into your lips as soon as it is applied.

Directions: After applying a thin layer of lipstick, another layer of clear lip gloss will allow an additional transparency